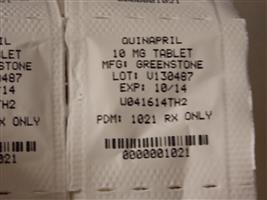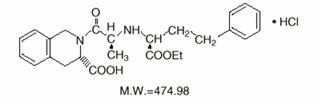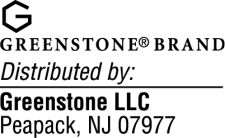 DRUG LABEL: Quinapril Hydrochloride
NDC: 68151-1021 | Form: TABLET, FILM COATED
Manufacturer: Carilion Materials Management
Category: prescription | Type: HUMAN PRESCRIPTION DRUG LABEL
Date: 20140613

ACTIVE INGREDIENTS: QUINAPRIL 10 mg/1 1
INACTIVE INGREDIENTS: CANDELILLA WAX; CROSPOVIDONE; GELATIN; LACTOSE; MAGNESIUM CARBONATE; MAGNESIUM STEARATE; FERRIC OXIDE RED; TITANIUM DIOXIDE

Quinapril Hydrochloride Tablets

WARNING: FETAL TOXICITY

- When pregnancy is detected, discontinue quinapril hydrochloride tablets as soon as possible.
- Drugs that act directly on the renin-angiotensin system can cause injury and death to the developing fetus. See Warnings: Fetal Toxicity

DESCRIPTION

Quinapril hydrochloride is the hydrochloride salt of quinapril, the ethyl ester of a non-sulfhydryl, angiotensin-converting enzyme (ACE) inhibitor, quinaprilat.

Quinapril hydrochloride is chemically described as [3S-[2[R*(R*)], 3R*]]-2-[2-[[1-(ethoxycarbonyl)-3-phenylpropyl]amino]-1-oxopropyl]-1,2,3,4-tetrahydro-3-isoquinolinecarboxylic acid, monohydrochloride. Its empirical formula is C H N O •HCl and its structural formula is:253025

Quinapril hydrochloride is a white to off-white amorphous powder that is freely soluble in aqueous solvents.

Quinapril hydrochloride tablets contain 5 mg, 10 mg, 20 mg, or 40 mg of quinapril for oral administration. Each tablet also contains candelilla wax, crospovidone, gelatin, lactose, magnesium carbonate, magnesium stearate, synthetic red iron oxide, and titanium dioxide.

CLINICAL PHARMACOLOGY

Mechanism of Action

Quinapril is deesterified to the principal metabolite, quinaprilat, which is an inhibitor of ACE activity in human subjects and animals. ACE is a peptidyl dipeptidase that catalyzes the conversion of angiotensin I to the vasoconstrictor, angiotensin II. The effect of quinapril in hypertension and in congestive heart failure (CHF) appears to result primarily from the inhibition of circulating and tissue ACE activity, thereby reducing angiotensin II formation. Quinapril inhibits the elevation in blood pressure caused by intravenously administered angiotensin I, but has no effect on the pressor response to angiotensin II, norepinephrine or epinephrine. Angiotensin II also stimulates the secretion of aldosterone from the adrenal cortex, thereby facilitating renal sodium and fluid reabsorption. Reduced aldosterone secretion by quinapril may result in a small increase in serum potassium. In controlled hypertension trials, treatment with quinapril hydrochloride alone resulted in mean increases in potassium of 0.07 mmol/L (see). Removal of angiotensin II negative feedback on renin secretion leads to increased plasma renin activity (PRA). PRECAUTIONS

While the principal mechanism of antihypertensive effect is thought to be through the renin-angiotensin-aldosterone system, quinapril exerts antihypertensive actions even in patients with low renin hypertension. Quinapril hydrochloride was an effective antihypertensive in all races studied, although it was somewhat less effective in blacks (usually a predominantly low renin group) than in nonblacks. ACE is identical to kininase II, an enzyme that degrades bradykinin, a potent peptide vasodilator; whether increased levels of bradykinin play a role in the therapeutic effect of quinapril remains to be elucidated.

Pharmacokinetics and Metabolism

Following oral administration, peak plasma quinapril concentrations are observed within one hour. Based on recovery of quinapril and its metabolites in urine, the extent of absorption is at least 60%. The rate and extent of quinapril absorption are diminished moderately (approximately 25–30%) when quinapril hydrochloride tablets are administered during a high-fat meal. Following absorption, quinapril is deesterified to its major active metabolite, quinaprilat (about 38% of oral dose), and to other minor inactive metabolites. Following multiple oral dosing of quinapril hydrochloride tablets , there is an effective accumulation half-life of quinaprilat of approximately 3 hours, and peak plasma quinaprilat concentrations are observed approximately 2 hours post-dose. Quinaprilat is eliminated primarily by renal excretion, up to 96% of an IV dose, and has an elimination half-life in plasma of approximately 2 hours and a prolonged terminal phase with a half-life of 25 hours. The pharmacokinetics of quinapril and quinaprilat are linear over a single-dose range of 5–80 mg doses and 40–160 mg in multiple daily doses. Approximately 97% of either quinapril or quinaprilat circulating in plasma is bound to proteins.

In patients with renal insufficiency, the elimination half-life of quinaprilat increases as creatinine clearance decreases. There is a linear correlation between plasma quinaprilat clearance and creatinine clearance. In patients with end-stage renal disease, chronic hemodialysis or continuous ambulatory peritoneal dialysis has little effect on the elimination of quinapril and quinaprilat. Elimination of quinaprilat may be reduced in elderly patients (≥65 years) and in those with heart failure; this reduction is attributable to decrease in renal function (see). Quinaprilat concentrations are reduced in patients with alcoholic cirrhosis due to impaired deesterification of quinapril. Studies in rats indicate that quinapril and its metabolites do not cross the blood-brain barrier. DOSAGE AND ADMINISTRATION

Pharmacodynamics and Clinical Effects

Hypertension

Single doses of 20 mg of quinapril hydrochloride tablets provide over 80% inhibition of plasma ACE for 24 hours. Inhibition of the pressor response to angiotensin I is shorter-lived, with a 20 mg dose giving 75% inhibition for about 4 hours, 50% inhibition for about 8 hours, and 20% inhibition at 24 hours. With chronic dosing, however, there is substantial inhibition of angiotensin II levels at 24 hours by doses of 20–80 mg.

Administration of 10 to 80 mg of quinapril hydrochloride tablets to patients with mild to severe hypertension results in a reduction of sitting and standing blood pressure to about the same extent with minimal effect on heart rate. Symptomatic postural hypotension is infrequent although it can occur in patients who are salt-and/or volume-depleted (see). Antihypertensive activity commences within 1 hour with peak effects usually achieved by 2 to 4 hours after dosing. During chronic therapy, most of the blood pressure lowering effect of a given dose is obtained in 1–2 weeks. In multiple-dose studies, 10–80 mg per day in single or divided doses lowered systolic and diastolic blood pressure throughout the dosing interval, with a trough effect of about 5–11/3–7 mm Hg. The trough effect represents about 50% of the peak effect. While the dose-response relationship is relatively flat, doses of 40–80 mg were somewhat more effective at trough than 10–20 mg, and twice daily dosing tended to give a somewhat lower trough blood pressure than once daily dosing with the same total dose. The antihypertensive effect of quinapril hydrochloride tablets continues during long-term therapy, with no evidence of loss of effectiveness. WARNINGS

Hemodynamic assessments in patients with hypertension indicate that blood pressure reduction produced by quinapril is accompanied by a reduction in total peripheral resistance and renal vascular resistance with little or no change in heart rate, cardiac index, renal blood flow, glomerular filtration rate, or filtration fraction.

Use of quinapril hydrochloride tablets with a thiazide diuretic gives a blood-pressure lowering effect greater than that seen with either agent alone.

In patients with hypertension, quinapril hydrochloride tablets 10–40 mg was similar in effectiveness to captopril, enalapril, propranolol, and thiazide diuretics.

Therapeutic effects appear to be the same for elderly (≥65 years of age) and younger adult patients given the same daily dosages, with no increase in adverse events in elderly patients.

Heart Failure

In a placebo-controlled trial involving patients with congestive heart failure treated with digitalis and diuretics, parenteral quinaprilat, the active metabolite of quinapril, reduced pulmonary capillary wedge pressure and systemic vascular resistance and increased cardiac output/index. Similar favorable hemodynamic effects were seen with oral quinapril in baseline-controlled trials, and such effects appeared to be maintained during chronic oral quinapril therapy. Quinapril reduced renal hepatic vascular resistance and increased renal and hepatic blood flow with glomerular filtration rate remaining unchanged.

A significant dose response relationship for improvement in maximal exercise tolerance has been observed with quinapril hydrochloride tablet therapy. Beneficial effects on the severity of heart failure as measured by New York Heart Association (NYHA) classification and Quality of Life and on symptoms of dyspnea, fatigue, and edema were evident after 6 months in a double-blind, placebo-controlled study. Favorable effects were maintained for up to two years of open label therapy. The effects of quinapril on long-term mortality in heart failure have not been evaluated.

INDICATIONS AND USAGE

Hypertension

Quinapril hydrochloride is indicated for the treatment of hypertension, to lower blood pressure. Lowering blood pressure reduces the risk of fatal and nonfatal cardiovascular events, primarily strokes and myocardial infarctions. These benefits have been seen in controlled trials of antihypertensive drugs from a wide variety of pharmacologic classes including the class to which this drug principally belongs. There are no controlled trials demonstrating risk reduction with quinapril hydrochloride.

Control of high blood pressure should be part of comprehensive cardiovascular risk management, including, as appropriate, lipid control, diabetes management, antithrombotic therapy, smoking cessation, exercise, and limited sodium intake. Many patients will require more than one drug to achieve blood pressure goals. For specific advice on goals and management, see published guidelines, such as those of the National High Blood Pressure Education Program's Joint National Committee on Prevention, Detection, Evaluation, and Treatment of High Blood Pressure (JNC).

Numerous antihypertensive drugs, from a variety of pharmacologic classes and with different mechanisms of action, have been shown in randomized controlled trials to reduce cardiovascular morbidity and mortality, and it can be concluded that it is blood pressure reduction, and not some other pharmacologic property of the drugs, that is largely responsible for those benefits. The largest and most consistent cardiovascular outcome benefit has been a reduction in the risk of stroke, but reductions in myocardial infarction and cardiovascular mortality also have been seen regularly.

Elevated systolic or diastolic pressure causes increased cardiovascular risk, and the absolute risk increase per mmHg is greater at higher blood pressures, so that even modest reductions of severe hypertension can provide substantial benefit. Relative risk reduction from blood pressure reduction is similar across populations with varying absolute risk, so the absolute benefit is greater in patients who are at higher risk independent of their hypertension (for example, patients with diabetes or hyperlipidemia), and such patients would be expected to benefit from more aggressive treatment to a lower blood pressure goal.

Some antihypertensive drugs have smaller blood pressure effects (as monotherapy) in black patients, and many antihypertensive drugs have additional approved indications and effects (e.g., on angina, heart failure, or diabetic kidney disease). These considerations may guide selection of therapy.

Quinapril hydrochloride may be used alone or in combination with thiazide diuretics.

Heart Failure

Quinapril hydrochloride tablets are indicated in the management of heart failure as adjunctive therapy when added to conventional therapy including diuretics and/or digitalis.

In using quinapril hydrochloride tablets, consideration should be given to the fact that another angiotensin-converting enzyme inhibitor, captopril, has caused agranulocytosis, particularly in patients with renal impairment or collagen vascular disease. Available data are insufficient to show that quinapril hydrochloride does not have a similar risk (see). WARNINGS

Angioedema in black patients

Black patients receiving ACE inhibitor monotherapy have been reported to have a higher incidence of angioedema compared to non-blacks. It should also be noted that in controlled clinical trials ACE inhibitors have an effect on blood pressure that is less in black patients than in non-blacks.

CONTRAINDICATIONS

Quinapril hydrochloride tablets are contraindicated in patients who are hypersensitive to this product and in patients with a history of angioedema related to previous treatment with an ACE inhibitor.

Do not co-administer quinapril hydrochloride tablets with aliskiren in patients with diabetes.

WARNINGS

Anaphylactoid and Possibly Related Reactions

Presumably because angiotensin-converting inhibitors affect the metabolism of eicosanoids and polypeptides, including endogenous bradykinin, patients receiving ACE inhibitors (including) may be subject to a variety of adverse reactions, some of them serious. quinapril hydrochloride

Head and Neck Angioedema

Angioedema of the face, extremities, lips, tongue, glottis, and larynx has been reported in patients treated with ACE inhibitors and has been seen in 0.1% of patients receiving quinapril hydrochloride tablets.

In two similarly sized U.S. postmarketing trials that, combined, enrolled over 3,000 black patients and over 19,000 non-blacks, angioedema was reported in 0.30% and 0.55% of blacks (in study 1 and 2 respectively) and 0.39% and 0.17% of non-blacks.

Angioedema associated with laryngeal edema can be fatal. If laryngeal stridor or angioedema of the face, tongue, or glottis occurs, treatment with quinapril hydrochloride tablets should be discontinued immediately, the patient treated in accordance with accepted medical care, and carefully observed until the swelling disappears. In instances where swelling is confined to the face and lips, the condition generally resolves without treatment; antihistamines may be useful in relieving symptoms. (see). Where there is involvement of the tongue, glottis, or larynx likely to cause airway obstruction, emergency therapy including, but not limited to, subcutaneous epinephrine solution 1:1000 (0.3 to 0.5 mL) should be promptly administered ADVERSE REACTIONS

Patients taking concomitant mTOR inhibitor (e.g. temsirolimus) therapy may be at increased risk for angioedema.

Intestinal Angioedema

Intestinal angioedema has been reported in patients treated with ACE inhibitors. These patients presented with abdominal pain (with or without nausea or vomiting); in some cases there was no prior history of facial angioedema and C-1 esterase levels were normal. The angioedema was diagnosed by procedures including abdominal CT scan or ultrasound, or at surgery, and symptoms resolved after stopping the ACE inhibitor. Intestinal angioedema should be included in the differential diagnosis of patients on ACE inhibitors presenting with abdominal pain.

Patients with a history of angioedema unrelated to ACE inhibitor therapy may be at increased risk of angioedema while receiving an ACE inhibitor (see also). CONTRAINDICATIONS

Anaphylactoid reactions during desensitization

Two patients undergoing desensitizing treatment with hymenoptera venom while receiving ACE inhibitors sustained life-threatening anaphylactoid reactions. In the same patients, these reactions were avoided when ACE inhibitors were temporarily withheld, but they reappeared upon inadvertent rechallenge.

Anaphylactoid reactions during membrane exposure

Anaphylactoid reactions have been reported in patients dialyzed with high-flux membranes and treated concomitantly with an ACE inhibitor. Anaphylactoid reactions have also been reported in patients undergoing low-density lipoprotein apheresis with dextran sulfate absorption.

Hepatic Failure

Rarely, ACE inhibitors have been associated with a syndrome that starts with cholestatic jaundice and progresses to fulminant hepatic necrosis and (sometimes) death. The mechanism of this syndrome is not understood. Patients receiving ACE inhibitors who develop jaundice or marked elevations of hepatic enzymes should discontinue the ACE inhibitor and receive appropriate medical follow-up.

Hypotension

Excessive hypotension is rare in patients with uncomplicated hypertension treated with quinapril hydrochloride tablets alone. Patients with heart failure given quinapril hydrochloride tablets commonly have some reduction in blood pressure, but discontinuation of therapy because of continuing symptomatic hypotension usually is not necessary when dosing instructions are followed. Caution should be observed when initiating therapy in patients with heart failure (see). In controlled studies, syncope was observed in 0.4% of patients (N=3203); this incidence was similar to that observed for captopril (1%) and enalapril (0.8%). DOSAGE AND ADMINISTRATION

Patients at risk of excessive hypotension, sometimes associated with oliguria and/or progressive azotemia, and rarely with acute renal failure and/or death, include patients with the following conditions or characteristics: heart failure, hyponatremia, high dose diuretic therapy, recent intensive diuresis or increase in diuretic dose, renal dialysis, or severe volume and/or salt depletion of any etiology. It may be advisable to eliminate the diuretic (except in patients with heart failure), reduce the diuretic dose or cautiously increase salt intake (except in patients with heart failure) before initiating therapy with quinapril hydrochloride tablets in patients at risk for excessive hypotension who are able to tolerate such adjustments.

In patients at risk of excessive hypotension, therapy with quinapril hydrochloride tablets should be started under close medical supervision. Such patients should be followed closely for the first two weeks of treatment and whenever the dose of quinapril hydrochloride tablets and/or diuretic is increased. Similar considerations may apply to patients with ischemic heart or cerebrovascular disease in whom an excessive fall in blood pressure could result in a myocardial infarction or a cerebrovascular accident.

If excessive hypotension occurs, the patient should be placed in the supine position and, if necessary, receive an intravenous infusion of normal saline. A transient hypotensive response is not a contraindication to further doses of quinapril hydrochloride tablets, which usually can be given without difficulty once the blood pressure has stabilized. If symptomatic hypotension develops, a dose reduction or discontinuation of quinapril hydrochloride tablets or concomitant diuretic may be necessary.

Neutropenia/Agranulocytosis

Another ACE inhibitor, captopril, has been shown to cause agranulocytosis and bone marrow depression rarely in patients with uncomplicated hypertension, but more frequently in patients with renal impairment, especially if they also have a collagen vascular disease, such as systemic lupus erythematosus or scleroderma. Agranulocytosis did occur during quinapril hydrochloride tablet treatment in one patient with a history of neutropenia during previous captopril therapy. Available data from clinical trials of quinapril hydrochloride tablets are insufficient to show that, in patients without prior reactions to other ACE inhibitors, quinapril hydrochloride does not cause agranulocytosis at similar rates. As with other ACE inhibitors, periodic monitoring of white blood cell counts in patients with collagen vascular disease and/or renal disease should be considered.

Fetal Toxicity

Pregnancy Category D

Use of drugs that act on the renin-angiotensin system during the second and third trimesters of pregnancy reduces fetal renal function and increases fetal and neonatal morbidity and death. Resulting oligohydramnios can be associated with fetal lung hypoplasia and skeletal deformations. Potential neonatal adverse effects include skull hypoplasia, anuria, hypotension, renal failure, and death. When pregnancy is detected, discontinue quinapril hydrochloride tablets as soon as possible. These adverse outcomes are usually associated with use of these drugs in the second and third trimester of pregnancy. Most epidemiologic studies examining fetal abnormalities after exposure to antihypertensive use in the first trimester have not distinguished drugs affecting the renin-angiotensin system from other antihypertensive agents. Appropriate management of maternal hypertension during pregnancy is important to optimize outcomes for both mother and fetus.

In the unusual case that there is no appropriate alternative to therapy with drugs affecting the renin-angiotensin system for a particular patient, apprise the mother of the potential risk to the fetus. Perform serial ultrasound examinations to assess the intra-amniotic environment. If oligohydramnios is observed, discontinue quinapril hydrochloride tablets, unless they are considered life-saving for the mother. Fetal testing may be appropriate, based on the week of pregnancy. Patients and physicians should be aware, however, that oligohydramnios may not appear until after the fetus has sustained irreversible injury. Closely observe infants with histories of exposure to quinapril hydrochloride tablets for hypotension, oliguria, and hyperkalemia (see). in utero PRECAUTIONS, Pediatric Use

No teratogenic effects of quinapril hydrochloride tablets were seen in studies of pregnant rats and rabbits. On a mg/kg basis, the doses used were up to 180 times (in rats) and one time (in rabbits) the maximum recommended human dose.

PRECAUTIONS

General

Impaired renal function

As a consequence of inhibiting the renin-angiotensin-aldosterone system, changes in renal function may be anticipated in susceptible individuals. In patients with severe heart failure whose renal function may depend on the activity of the renin-angiotensin-aldosterone system, treatment with ACE inhibitors, including quinapril hydrochloride tablets, may be associated with oliguria and/or progressive azotemia and rarely acute renal failure and/or death.

In clinical studies in hypertensive patients with unilateral or bilateral renal artery stenosis, increases in blood urea nitrogen and serum creatinine have been observed in some patients following ACE inhibitor therapy. These increases were almost always reversible upon discontinuation of the ACE inhibitor and/or diuretic therapy. In such patients, renal function should be monitored during the first few weeks of therapy.

Some patients with hypertension or heart failure with no apparent preexisting renal vascular disease have developed increases in blood urea and serum creatinine, usually minor and transient, especially when quinapril hydrochloride has been given concomitantly with a diuretic. This is more likely to occur in patients with preexisting renal impairment. Dosage reduction and/or discontinuation of any diuretic and/or quinapril hydrochloride tablets may be required.

(see). Evaluation of patients with hypertension or heart failure should always include assessment of renal function DOSAGE AND ADMINISTRATION

Hyperkalemia and potassium-sparing diuretics

In clinical trials, hyperkalemia (serum potassium ≥5.8 mmol/L) occurred in approximately 2% of patients receiving quinapril hydrochloride tablets . In most cases, elevated serum potassium levels were isolated values which resolved despite continued therapy. Less than 0.1% of patients discontinued therapy due to hyperkalemia. Risk factors for the development of hyperkalemia include renal insufficiency, diabetes mellitus, and the concomitant use of potassium-sparing diuretics, potassium supplements, and/or potassium-containing salt substitutes, which should be used cautiously, if at all, with quinapril hydrochloride tablets (see). PRECAUTIONS, Drug Interactions

Cough

Presumably due to the inhibition of the degradation of endogenous bradykinin, persistent non-productive cough has been reported with all ACE inhibitors, always resolving after discontinuation of therapy. ACE inhibitor-induced cough should be considered in the differential diagnosis of cough.

Surgery/anesthesia

In patients undergoing major surgery or during anesthesia with agents that produce hypotension, quinapril hydrochloride will block angiotensin II formation secondary to compensatory renin release. If hypotension occurs and is considered to be due to this mechanism, it can be corrected by volume expansion.

Information for Patients

Pregnancy

Female patients of childbearing age should be told about the consequences of exposure to quinapril hydrochloride tablets during pregnancy. Discuss treatment options with women planning to become pregnant. Patients should be asked to report pregnancies to their physicians as soon as possible.

Angioedema

Angioedema, including laryngeal edema can occur with treatment with ACE inhibitors, especially following the first dose. Patients should be so advised and told to report immediately any signs or symptoms suggesting angioedema (swelling of face, extremities, eyes, lips, tongue, difficulty in swallowing or breathing) and to stop taking the drug until they have consulted with their physician (see). WARNINGS

Symptomatic hypotension

Patients should be cautioned that lightheadedness can occur, especially during the first few days of quinapril hydrochloride tablet therapy, and that it should be reported to a physician. If actual syncope occurs, patients should be told to not take the drug until they have consulted with their physician (see). WARNINGS

All patients should be cautioned that inadequate fluid intake or excessive perspiration, diarrhea, or vomiting can lead to an excessive fall in blood pressure because of reduction in fluid volume, with the same consequences of lightheadedness and possible syncope.

Patients planning to undergo any surgery and/or anesthesia should be told to inform their physician that they are taking an ACE inhibitor.

Hyperkalemia

Patients should be told not to use potassium supplements or salt substitutes containing potassium without consulting their physician (see). PRECAUTIONS

Neutropenia

Patients should be told to report promptly any indication of infection (eg, sore throat, fever) which could be a sign of neutropenia.

NOTE: As with many other drugs, certain advice to patients being treated with quinapril hydrochloride tablets is warranted. This information is intended to aid in the safe and effective use of this medication. It is not a disclosure of all possible adverse or intended effects.

Drug Interactions

Concomitant diuretic therapy

As with other ACE inhibitors, patients on diuretics, especially those on recently instituted diuretic therapy, may occasionally experience an excessive reduction of blood pressure after initiation of therapy with quinapril hydrochloride tablets. The possibility of hypotensive effects with quinapril hydrochloride tablets may be minimized by either discontinuing the diuretic or cautiously increasing salt intake prior to initiation of treatment with quinapril hydrochloride tablets. If it is not possible to discontinue the diuretic, the starting dose of quinapril should be reduced (see). DOSAGE AND ADMINISTRATION

Agents increasing serum potassium

Quinapril can attenuate potassium loss caused by thiazide diuretics and increase serum potassium when used alone. If concomitant therapy of quinapril hydrochloride tablets with potassium-sparing diuretics (eg, spironolactone, triamterene, or amiloride), potassium supplements, or potassium-containing salt substitutes is indicated, they should be used with caution along with appropriate monitoring of serum potassium (see). PRECAUTIONS

Tetracycline and other drugs that interact with magnesium

Simultaneous administration of tetracycline with quinapril hydrochloride tablets reduced the absorption of tetracycline by approximately 28% to 37%, possibly due to the high magnesium content in quinapril hydrochloride tablets. This interaction should be considered if coprescribing quinapril hydrochloride and tetracycline or other drugs that interact with magnesium.

Lithium

Increased serum lithium levels and symptoms of lithium toxicity have been reported in patients receiving concomitant lithium and ACE inhibitor therapy. These drugs should be coadministered with caution and frequent monitoring of serum lithium levels is recommended. If a diuretic is also used, it may increase the risk of lithium toxicity.

Gold

Nitritoid reactions (symptoms include facial flushing, nausea, vomiting, and hypotension) have been reported rarely in patients on therapy with injectable gold (sodium aurothiomalate) and concomitant ACE inhibitor therapy.

Non-steroidal anti-inflammatory agents including selective cyclooxygenase-2 inhibitors (COX-2 inhibitors)

In patients who are elderly, volume-depleted (including those on diuretic therapy), or with compromised renal function, co-administration of NSAIDs, including selective COX-2 inhibitors, with ACE inhibitors, including quinapril, may result in deterioration of renal function, including possible acute renal failure. These effects are usually reversible. Monitor renal function periodically in patients receiving quinapril and NSAID therapy.

The antihypertensive effect of ACE inhibitors, including quinapril may be attenuated by NSAIDs.

Agents that inhibit mTOR

Patients taking concomitant mTOR inhibitor (e.g. temsirolimus) therapy may be at increased risk for angioedema.

Other agents

Drug interaction studies of quinapril hydrochloride with other agents showed:

- Multiple dose therapy with propranolol or cimetidine has no effect on the pharmacokinetics of single doses of quinapril hydrochloride tablets.
- The anticoagulant effect of a single dose of warfarin (measured by prothrombin time) was not significantly changed by quinapril coadministration twice-daily.
- Quinapril hydrochloride tablet treatment did not affect the pharmacokinetics of digoxin.
- No pharmacokinetic interaction was observed when single doses of quinapril hydrochloride and hydrochlorothiazide were administered concomitantly.
- Co-administration of multiple 10 mg doses of atorvastatin with 80 mg of quinapril hydrochloride resulted in no significant change in the steady-state pharmacokinetic parameters of atorvastatin.

Dual Blockade of the Renin-Angiotensin System (RAS)

Dual blockade of the RAS with angiotensin receptor blockers, ACE inhibitors, or aliskiren is associated with increased risks of hypotension, hyperkalemia, and changes in renal function (including acute renal failure) compared to monotherapy. Most patients receiving the combination of two RAS inhibitors do not obtain any additional benefit compared to monotherapy. In general, avoid combined use of RAS inhibitors. Closely monitor blood pressure, renal function and electrolytes in patients on quinapril hydrochloride tablets and other agents that affect the RAS.

Do not co-administer aliskiren with Quinapril hydrochloride tablets in patients with diabetes. Avoid concomitant use of aliskiren with quinapril hydrochloride tablets in patients with renal impairment (GFR <60 mL/min/1.73 m).^2

Carcinogenesis, Mutagenesis, Impairment of Fertility

Quinapril hydrochloride was not carcinogenic in mice or rats when given in doses up to 75 or 100 mg/kg/day (50 to 60 times the maximum human daily dose, respectively, on an mg/kg basis and 3.8 to 10 times the maximum human daily dose when based on an mg/m basis) for 104 weeks. Female rats given the highest dose level had an increased incidence of mesenteric lymph node hemangiomas and skin/subcutaneous lipomas. Neither quinapril nor quinaprilat were mutagenic in the Ames bacterial assay with or without metabolic activation. Quinapril was also negative in the following genetic toxicology studies: mammalian cell point mutation, sister chromatid exchange in cultured mammalian cells, micronucleus test with mice, chromosome aberration with V79 cultured lung cells, and in an cytogenetic study with rat bone marrow. There were no adverse effects on fertility or reproduction in rats at doses up to 100 mg/kg/day (60 and 10 times the maximum daily human dose when based on mg/kg and mg/m , respectively).^2 in vitroin vitroin vivo^2

Nursing Mothers

Because quinapril hydrochloride is secreted in human milk, caution should be exercised when this drug is administered to a nursing woman.

Pediatric Use

Neonates with a history of exposure to quinapril hydrochloride tablets in utero

If oliguria or hypotension occurs, direct attention toward support of blood pressure and renal perfusion. Exchange transfusions or dialysis may be required as a means of reversing hypotension and/or substituting for disordered renal function. Removal of quinapril hydrochloride tablets, which cross the placenta, from the neonatal circulation is not significantly accelerated by these means.

The safety and effectiveness of quinapril hydrochloride in pediatric patients have not been established.

Geriatric Use

Clinical studies of quinapril hydrochloride tablets did not include sufficient numbers of subjects aged 65 and over to determine whether they respond differently from younger subjects. Other reported clinical experience has not identified differences in responses between the elderly and younger patients. In general, dose selection for an elderly patient should be cautious, usually starting at the low end of the dosing range, reflecting the greater frequency of decreased hepatic, renal or cardiac function, and of concomitant disease or other drug therapy.

This drug is known to be substantially excreted by the kidney, and the risk of toxic reactions to this drug may be greater in patients with impaired renal function. Because elderly patients are more likely to have decreased renal function, care should be taken in dose selection, and it may be useful to monitor renal function.

Elderly patients exhibited increased area under the plasma concentration time curve and peak levels for quinaprilat compared to values observed in younger patients; this appeared to relate to decreased renal function rather than to age itself.

ADVERSE REACTIONS

Hypertension

Quinapril hydrochloride tablets have been evaluated for safety in 4960 subjects and patients. Of these, 3203 patients, including 655 elderly patients, participated in controlled clinical trials. Quinapril hydrochloride tablets have been evaluated for long-term safety in over 1400 patients treated for 1 year or more.

Adverse experiences were usually mild and transient.

In placebo-controlled trials, discontinuation of therapy because of adverse events was required in 4.7% of patients with hypertension.

Adverse experiences probably or possibly related to therapy or of unknown relationship to therapy occurring in 1% or more of the 1563 patients in placebo-controlled hypertension trials who were treated with quinapril hydrochloride tablets are shown below.

Adverse Events in Placebo-Controlled Trials
 | Quinapril HCl (N=1563) Incidence (Discontinuance) | Placebo (N=579) Incidence (Discontinuance)
Headache | 5.6 (0.7) | 10.9 (0.7)
Dizziness | 3.9 (0.8) | 2.6 (0.2)
Fatigue | 2.6 (0.3) | 1.0
Coughing | 2.0 (0.5) | 0.0
Nausea and/or Vomiting | 1.4 (0.3) | 1.9 (0.2)
Abdominal Pain | 1.0 (0.2) | 0.7

Heart Failure

Quinapril hydrochloride tablets have been evaluated for safety in 1222 quinapril hydrochloride treated patients. Of these, 632 patients participated in controlled clinical trials. In placebo-controlled trials, discontinuation of therapy because of adverse events was required in 6.8% of patients with congestive heart failure.

Adverse experiences probably or possibly related or of unknown relationship to therapy occurring in 1% or more of the 585 patients in placebo-controlled congestive heart failure trials who were treated with quinapril hydrochloride tablets are shown below.

 | Quinapril HCl (N=585) Incidence (Discontinuance) | Placebo (N=295) Incidence (Discontinuance)
Dizziness | 7.7 (0.7) | 5.1 (1.0)
Coughing | 4.3 (0.3) | 1.4
Fatigue | 2.6 (0.2) | 1.4
Nausea and/or Vomiting | 2.4 (0.2) | 0.7
Chest Pain | 2.4 | 1.0
Hypotension | 2.9 (0.5) | 1.0
Dyspnea | 1.9 (0.2) | 2.0
Diarrhea | 1.7 | 1.0
Headache | 1.7 | 1.0 (0.3)
Myalgia | 1.5 | 2.0
Rash | 1.4 (0.2) | 1.0
Back Pain | 1.2 | 0.3

See . PRECAUTIONS, Cough

Hypertension and/or Heart Failure

Clinical adverse experiences probably, possibly, or definitely related, or of uncertain relationship to therapy occurring in 0.5% to 1.0% (except as noted) of the patients with CHF or hypertension treated with quinapril hydrochloride tablets (with or without concomitant diuretic) in controlled or uncontrolled trials (N=4847) and less frequent, clinically significant events seen in clinical trials or post-marketing experience (the rarer events are in italics) include (listed by body system):

back pain, malaise, viral infections, General: anaphylactoid reaction

palpitation, vasodilation, tachycardia, Cardiovascular: heart failure, hyperkalemia, myocardial infarction, cerebrovascular accident, hypertensive crisis, angina pectoris, orthostatic hypotension, cardiac rhythm disturbances, cardiogenic shock

Hematology: hemolytic anemia

flatulence, dry mouth or throat, constipation, Gastrointestinal: gastrointestinal hemorrhage, pancreatitis, abnormal liver function tests, dyspepsia

somnolence, vertigo, syncope, nervousness, depression, insomnia, paresthesia Nervous/Psychiatric:

alopecia, increased sweating, pemphigus, pruritus, Integumentary: exfoliative dermatitis, photosensitivity reaction, dermatopolymyositis

urinary tract infection, impotence, Urogenital: acute renal failure, worsening renal failure

Respiratory: eosinophilic pneumonitis

amblyopia, edema, arthralgia, pharyngitis, Other: agranulocytosis, hepatitis, thrombocytopenia

Angioedema

Angioedema has been reported in patients receiving quinapril hydrochloride tablets (0.1%). Angioedema associated with laryngeal edema may be fatal. If angioedema of the face, extremities, lips, tongue, glottis, and/or larynx occurs, treatment with quinapril hydrochloride tablets should be discontinued and appropriate therapy instituted immediately. (see .) WARNINGS

Clinical Laboratory Test Findings

Hematology

(see) WARNINGS

Hyperkalemia

(see) PRECAUTIONS

Creatinine and Blood Urea Nitrogen

Increases (>1.25 times the upper limit of normal) in serum creatinine and blood urea nitrogen were observed in 2% and 2%, respectively, of all patients treated with quinapril hydrochloride tablets alone. Increases are more likely to occur in patients receiving concomitant diuretic therapy than in those on quinapril hydrochloride tablets alone. These increases often remit on continued therapy. In controlled studies of heart failure, increases in blood urea nitrogen and serum creatinine were observed in 11% and 8%, respectively, of patients treated with quinapril hydrochloride tablets; most often these patients were receiving diuretics with or without digitalis.

OVERDOSAGE

Doses of 1440 to 4280 mg/kg of quinapril cause significant lethality in mice and rats.

No specific information is available on the treatment of overdosage with quinapril. The most likely clinical manifestation would be symptoms attributable to severe hypotension.

Laboratory determinations of serum levels of quinapril and its metabolites are not widely available, and such determinations have, in any event, no established role in the management of quinapril overdose.

No data are available to suggest physiological maneuvers (eg, maneuvers to change pH of the urine) that might accelerate elimination of quinapril and its metabolites.

Hemodialysis and peritoneal dialysis have little effect on the elimination of quinapril and quinaprilat. Angiotensin II could presumably serve as a specific antagonist-antidote in the setting of quinapril overdose, but angiotensin II is essentially unavailable outside of scattered research facilities. Because the hypotensive effect of quinapril is achieved through vasodilation and effective hypovolemia, it is reasonable to treat quinapril overdose by infusion of normal saline solution.

DOSAGE AND ADMINISTRATION

Hypertension

Monotherapy

The recommended initial dosage of quinapril hydrochloride tablets in patients not on diuretics is 10 or 20 mg once daily. Dosage should be adjusted according to blood pressure response measured at peak (2–6 hours after dosing) and trough (predosing). Generally, dosage adjustments should be made at intervals of at least 2 weeks. Most patients have required dosages of 20, 40, or 80 mg/day, given as a single dose or in two equally divided doses. In some patients treated once daily, the antihypertensive effect may diminish toward the end of the dosing interval. In such patients an increase in dosage or twice daily administration may be warranted. In general, doses of 40–80 mg and divided doses give a somewhat greater effect at the end of the dosing interval.

Concomitant Diuretics

If blood pressure is not adequately controlled with quinapril hydrochloride monotherapy, a diuretic may be added. In patients who are currently being treated with a diuretic, symptomatic hypotension occasionally can occur following the initial dose of quinapril hydrochloride tablets. To reduce the likelihood of hypotension, the diuretic should, if possible, be discontinued 2 to 3 days prior to beginning therapy with quinapril hydrochloride tablets (see). Then, if blood pressure is not controlled with quinapril hydrochloride tablets alone, diuretic therapy should be resumed. WARNINGS

If the diuretic cannot be discontinued, an initial dose of 5 mg quinapril hydrochloride should be used with careful medical supervision for several hours and until blood pressure has stabilized.

The dosage should subsequently be titrated (as described above) to the optimal response (see , , and). WARNINGSPRECAUTIONSDrug Interactions

Renal Impairment

Kinetic data indicate that the apparent elimination half-life of quinaprilat increases as creatinine clearance decreases. Recommended starting doses, based on clinical and pharmacokinetic data from patients with renal impairment, are as follows:

Creatinine Clearance | Maximum Recommended Initial Dose
>60 mL/min | 10 mg
30–60 mL/min | 5 mg
10–30 mL/min | 2.5 mg
<10 mL/min | Insufficient data for dosage recommendation

Patients should subsequently have their dosage titrated (as described above) to the optimal response.

Elderly (≥65 years)

The recommended initial dosage of quinapril hydrochloride tablets in elderly patients is 10 mg given once daily followed by titration (as described above) to the optimal response.

Heart Failure

Quinapril hydrochloride tablets are indicated as adjunctive therapy when added to conventional therapy including diuretics and/or digitalis. The recommended starting dose is 5 mg twice daily. This dose may improve symptoms of heart failure, but increases in exercise duration have generally required higher doses. Therefore, if the initial dosage of quinapril hydrochloride tablets is well tolerated, patients should then be titrated at weekly intervals until an effective dose, usually 20 to 40 mg daily given in two equally divided doses, is reached or undesirable hypotension, orthostatis, or azotemia (see) prohibit reaching this dose. WARNINGS

Following the initial dose of quinapril hydrochloride tablets, the patient should be observed under medical supervision for at least two hours for the presence of hypotension or orthostatis and, if present, until blood pressure stabilizes. The appearance of hypotension, orthostatis, or azotemia early in dose titration should not preclude further careful dose titration. Consideration should be given to reducing the dose of concomitant diuretics.

DOSE ADJUSTMENTS IN PATIENTS WITH HEART FAILURE AND RENAL IMPAIRMENT OR HYPONATREMIA

Pharmacokinetic data indicate that quinapril elimination is dependent on level of renal function. In patients with heart failure and renal impairment, the recommended initial dose of quinapril hydrochloride tablets is 5 mg in patients with a creatinine clearance above 30 mL/min and 2.5 mg in patients with a creatinine clearance of 10 to 30 mL/min. There is insufficient data for dosage recommendation in patients with a creatinine clearance less than 10 mL/min (see , , and). DOSAGE AND ADMINISTRATION, Heart Failure WARNINGSPRECAUTIONS, Drug Interactions

If the initial dose is well tolerated, quinapril hydrochloride tablets may be administered the following day as a twice daily regimen. In the absence of excessive hypotension or significant deterioration of renal function, the dose may be increased at weekly intervals based on clinical and hemodynamic response.

HOW SUPPLIED

NDC:68151-1021-1 in a PACKAGE of 1 TABLET, FILM COATEDS

Storage

Store at controlled room temperature 15º–30ºC (59º–86ºF).

Protect from light.

LAB-0349-12.0 Revised June 2014